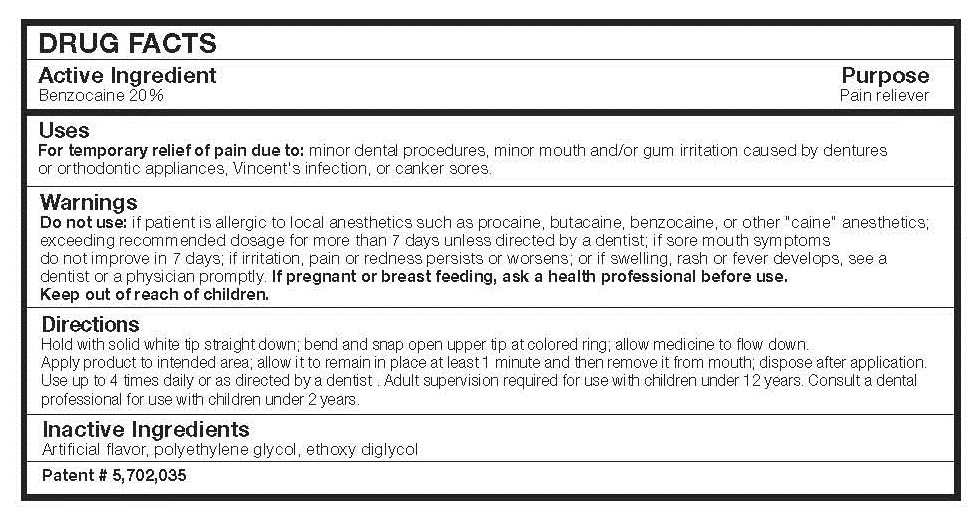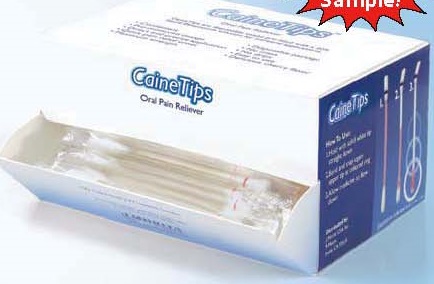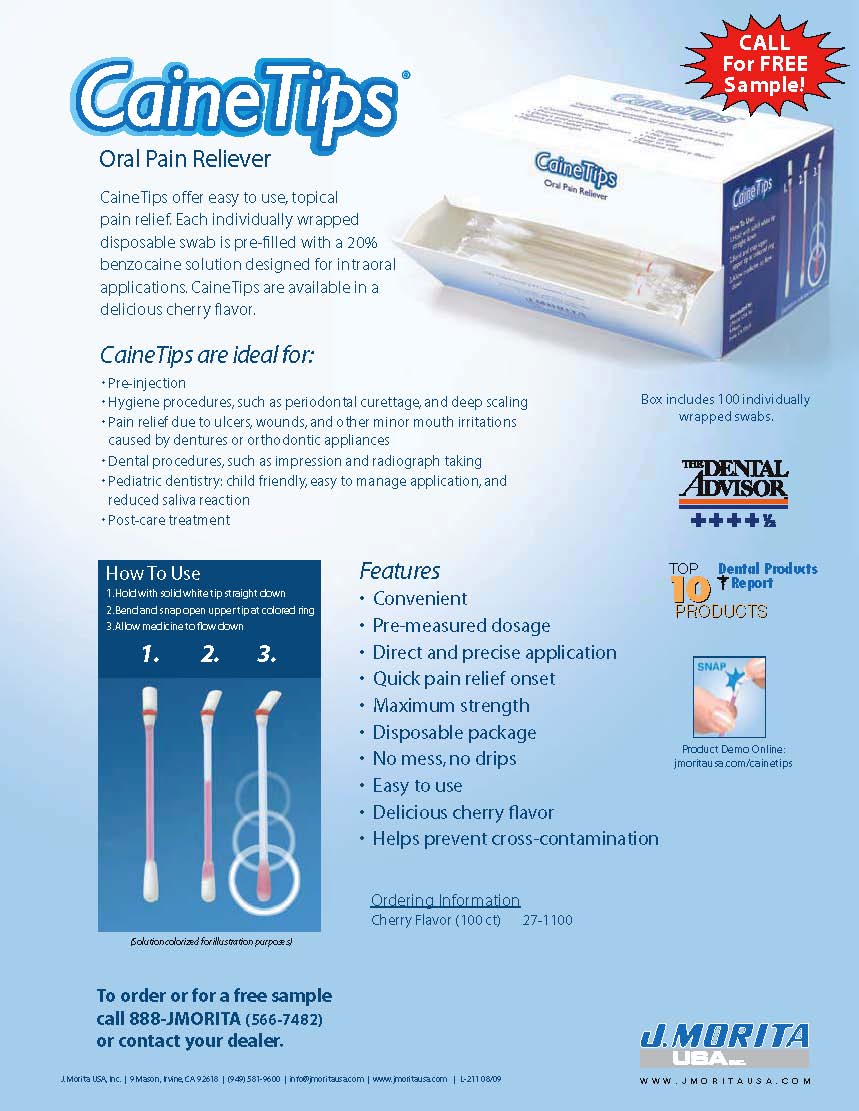 DRUG LABEL: CaineTips
NDC: 70769-101 | Form: LIQUID
Manufacturer: J MORITA USA INC
Category: otc | Type: HUMAN OTC DRUG LABEL
Date: 20230922

ACTIVE INGREDIENTS: BENZOCAINE 20 g/100 mL
INACTIVE INGREDIENTS: POLYETHYLENE GLYCOL 1000; DIETHYLENE GLYCOL MONOETHYL ETHER

J MORITA USA - CAINE TIPS (70769-101)

ACTIVE INGREDIENT

BENZOCAINE 20%

PURPOSE

PAIN RELIEVER

USES

For temporary relief of pain due to: minor dental procedures, minor mouth and/or gum irritation caused by dentures or orthodontic appliances, Vincent's infection, or canker sores.

WARNINGS

Do not use: if patient is allergic to local anesthetics such as procaine, butacaine, benzocaine, or other "caine" anesthetics;
exceeding recommended dosage for more than 7 days unless directed by a dentist; if sore mouth symptoms
do not improve in 7 days; if irritation, pain or redness persists or worsens; or if swelling, rash or fever develops, see a
dentist or a physician promptly.

PREGNANCY

If pregnant or breast feeding, ask a health professional before use.

Keep out of reach of children.

DIRECTIONS

HOLD WITH SOLID WHITE TIP STRAIGHT DOWN; BEND AND SNAP OPEN UPPER TIP AT COLORED RING; ALLOW MEDICINE TO FLOW DOWN.

APPLY PRODUCT TO INTENDED AREA; ALLOW IT TO REMAIN IN PLACE AT LEAST 1 MINUTE AND THEN REMOVE IT FROM MOUTH; DISPOSE AFTER APPLICATION.

USE UP TO 4 TIMES DAILY, OR AS DIRECTED BY A DENTIST. ADULT SUPERVISION REQUIRED FOR USE WITH CHILDREN UNDER 12 YEARS. CONSULT A DENTAL PROFESSIONAL FOR USE WITH CHILDREN UNDER 2 YEARS.

INACTIVE INGREDIENTS

ARTIFICIAL FLAVOR, POLYETHYLENE GLYCOL, ETHOXY DIGLYCOL